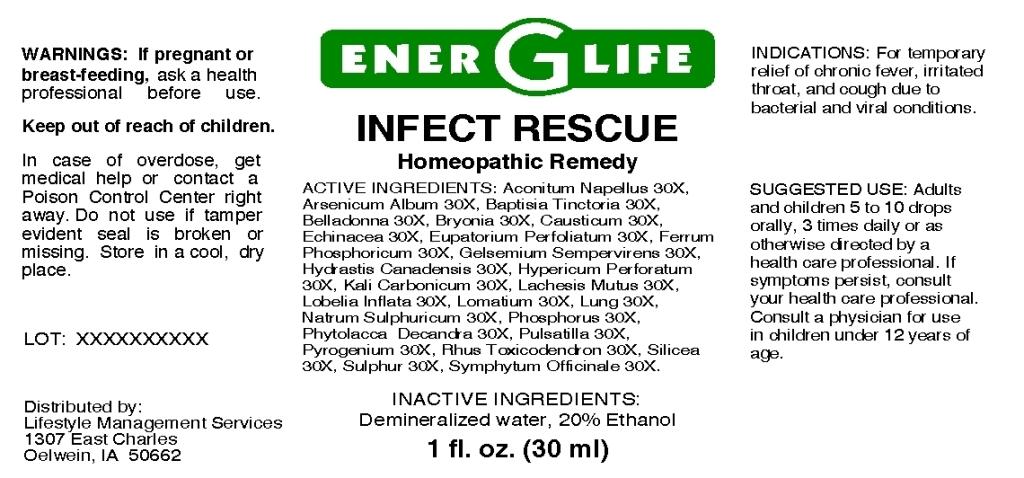 DRUG LABEL: Infect Rescue
NDC: 57520-0662 | Form: LIQUID
Manufacturer: Apotheca Company
Category: homeopathic | Type: HUMAN OTC DRUG LABEL
Date: 20110401

ACTIVE INGREDIENTS: ACONITUM NAPELLUS 30 [hp_X]/1 mL; ARSENIC TRIOXIDE 30 [hp_X]/1 mL; BAPTISIA TINCTORIA ROOT 30 [hp_X]/1 mL; ATROPA BELLADONNA 30 [hp_X]/1 mL; BRYONIA ALBA ROOT 30 [hp_X]/1 mL; CAUSTICUM 30 [hp_X]/1 mL; ECHINACEA 30 [hp_X]/1 mL; EUPATORIUM PERFOLIATUM FLOWERING TOP 30 [hp_X]/1 mL; FERRUM PHOSPHORICUM 30 [hp_X]/1 mL; GELSEMIUM SEMPERVIRENS ROOT 30 [hp_X]/1 mL; GOLDENSEAL 30 [hp_X]/1 mL; HYPERICUM PERFORATUM 30 [hp_X]/1 mL; POTASSIUM CARBONATE 30 [hp_X]/1 mL; LACHESIS MUTA VENOM 30 [hp_X]/1 mL; LOBELIA INFLATA 30 [hp_X]/1 mL; LOMATIUM DISSECTUM ROOT 30 [hp_X]/1 mL; SODIUM SULFATE 30 [hp_X]/1 mL; PHOSPHORUS 30 [hp_X]/1 mL; PHYTOLACCA AMERICANA ROOT 30 [hp_X]/1 mL; PULSATILLA VULGARIS 30 [hp_X]/1 mL; RANCID BEEF 30 [hp_X]/1 mL; TOXICODENDRON PUBESCENS LEAF 30 [hp_X]/1 mL; SILICON DIOXIDE 30 [hp_X]/1 mL; SULFUR 30 [hp_X]/1 mL; COMFREY ROOT 30 [hp_X]/1 mL; DEFIBROTIDE (BOVINE LUNG) 30 [hp_X]/1 mL
INACTIVE INGREDIENTS: WATER; ALCOHOL

Infect Rescue

ACTIVE INGREDIENT

ACTIVE INGREDIENTS: Aconitum napellus 30X, Arsenicum album 30X, Baptisia tinctoria 30X, Belladonna 30X, Bryonia 30X, Causticum 30X, Echinacea 30X, Eupatorium perfoliatum 30X, Ferrum phosphoricum 30X, Gelsemium sempervirens 30X, Hydrastis canadensis 30X, Hypericum perforatum 30X, Kali carbonicum 30X, Lachesis mutus 30X, Lobelia inflata 30X, Lomatium 30X, Lung 30X, Natrum sulphuricum 30X, Phosphorus 30X, Phytolacca decandra 30X, Pulsatilla 30X, Pyrogenium 30X, Rhus toxicodendron 30X, Silicea 30X, Sulphur 30X, Symphytum officinale 30X.

PURPOSE

INDICATIONS: For temporary relief of chronic fever, irritated throat, and cough due to bacterial and viral conditions.

WARNINGS

WARNINGS: If pregnant or breast-feeding, ask a health professional before use.

Keep out of reach of children. In case of overdose, get medical help or contact a Poison Control Center right away.

Do not use if tamper evident seal is broken or missing. Store in a cool, dry place.

DOSAGE AND ADMINISTRATION

SUGGESTED USE: Adults and children 5 to 10 drops orally, 3 times daily or as otherwise directed by a health care professional. If symptoms persist, consult your health care professional. Consult a physician for use in children under 12 years of age.

INACTIVE INGREDIENTS: Demineralized water, 20% Ethanol.

KEEP OUT OF REACH OF CHILDREN. In case of overdose, get medical help or contact a Poison Control Center right away.

INDICATIONS AND USAGE

INDICATIONS: For temporary relief of chronic fever, irritated throat, and cough due to bacterial and viral conditions.

QUESTIONS

Distributed by:

Lifestyle Management Services

1307 East Charles

Oelwein, IA 50662

PACKAGE LABEL

ENER G LIFE

INFECT RESCUE

Homeopathic Remedy

1 fl. oz. (30 ml)